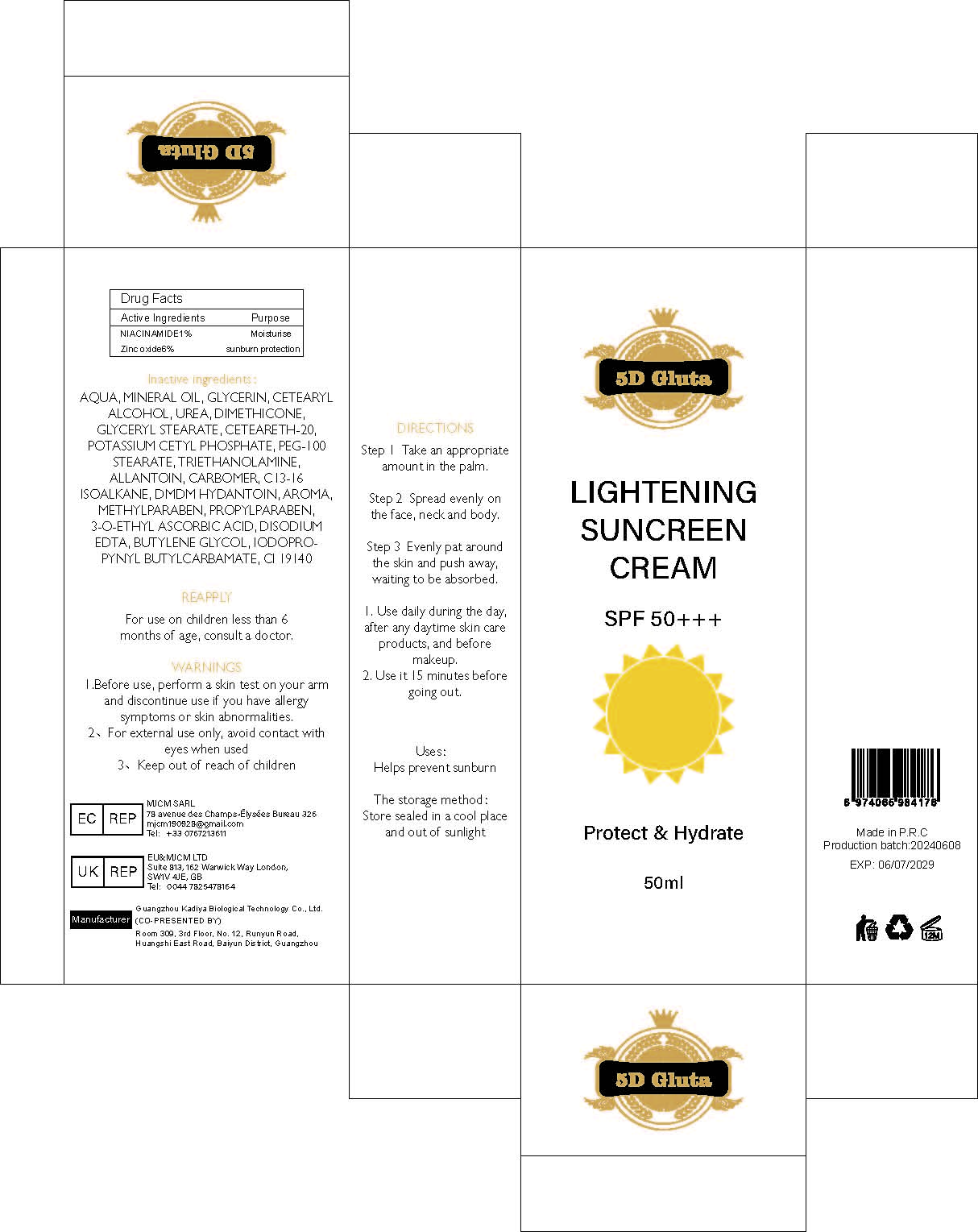 DRUG LABEL: Lightening Suncreen Cream
NDC: 84423-010 | Form: EMULSION
Manufacturer: Guangzhou Kadiya Biotechnology Co., Ltd.
Category: otc | Type: HUMAN OTC DRUG LABEL
Date: 20240708

ACTIVE INGREDIENTS: NIACINAMIDE 0.5 mg/50 mg; ZINC OXIDE 3 mg/50 mg
INACTIVE INGREDIENTS: POLYOXYL 20 CETOSTEARYL ETHER; POTASSIUM CETYL PHOSPHATE; MINERAL OIL; DIMETHICONE; IODOPROPYNYL BUTYLCARBAMATE; DMDM HYDANTOIN; CARBOMER HOMOPOLYMER, UNSPECIFIED TYPE; EDETATE DISODIUM; WATER; UREA; GLYCERYL MONOSTEARATE; PROPYLPARABEN; C13-16 ISOPARAFFIN; FD&C YELLOW NO. 5; ALLANTOIN; 3-O-ETHYL ASCORBIC ACID; CETOSTEARYL ALCOHOL; PEG-100 STEARATE; TROLAMINE; GLYCERIN; BUTYLENE GLYCOL; METHYLPARABEN

Uses：
Helps prevent sunburn
Indications: For sun protection

INACTIVE INGREDIENT

AQUA、MINERAL OIL、GLYCERIN、CETEARYL ALCOHOL、UREA、DIMETHICONE、GLYCERYL STEARATE、CETEARETH-20、POTASSIUM CETYL PHOSPHATE、PEG-100 STEARATE、TRIETHANOLAMINE、ALLANTOIN、CARBOMER、C13-16 ISOALKANE、DMDM HYDANTOIN、AROMA、METHYLPARABEN、PROPYLPARABEN、3-O-ETHYL ASCORBIC ACID、DISODIUM EDTA、BUTYLENE GLYCOL、IODOPROPYNYL BUTYLCARBAMATE、CI 19140

Warning.
1.Before use, perform a skin test on your arm and discontinue use if you have allergy symptoms or skin abnormalities.
2、For external use only, avoid contact with eyes when used
3、Keep out of reach of children

INDICATIONS AND USAGE

Step 1 Take an appropriate
amount in the palm.
Step 2 Spread evenly on
the face, neck and body.
Step 3 Evenly pat around
the skin and push away,
waiting to be absorbed.
1. Use daily during the day,
after any daytime skin care
products, and before
makeup.
2. Use it 15 minutes before
going out.

KEEP OUT OF REACH OF CHILDREN SECTION

Active Ingredients
NIACINAMIDE 1mg
Zinc oxide 6%

DOSAGE AND ADMINISTRATION

1. Use daily during the day,
after any daytime skin care
products, and before
makeup.
2. Use it 15 minutes before
going out.

PACKAGE LABEL

Active Ingredients
NIACINAMIDE 1mg
Zinc oxide 6%

Uses：
Helps prevent sunburn
Indications: For sun protection

The storage method：
Store sealed in a cool place and out of sunlight

Warning.
1.Before use, perform a skin test on your arm and discontinue use if you have allergy symptoms or skin abnormalities.
2、For external use only, avoid contact with eyes when used
3、Keep out of reach of children

Inactive ingredients：
AQUA、MINERAL OIL、GLYCERIN、CETEARYL ALCOHOL、UREA、DIMETHICONE、GLYCERYL STEARATE、CETEARETH-20、POTASSIUM CETYL PHOSPHATE、PEG-100 STEARATE、TRIETHANOLAMINE、ALLANTOIN、CARBOMER、C13-16 ISOALKANE、DMDM HYDANTOIN、AROMA、METHYLPARABEN、PROPYLPARABEN、3-O-ETHYL ASCORBIC ACID、DISODIUM EDTA、BUTYLENE GLYCOL、IODOPROPYNYL BUTYLCARBAMATE、CI 19140